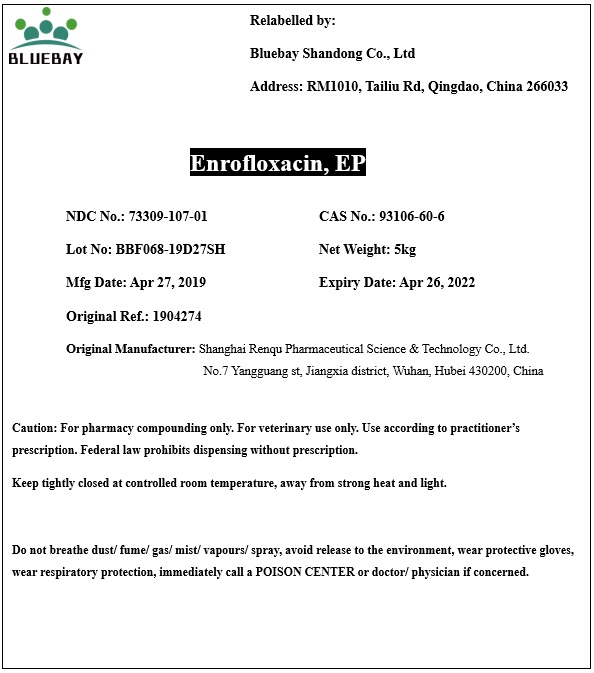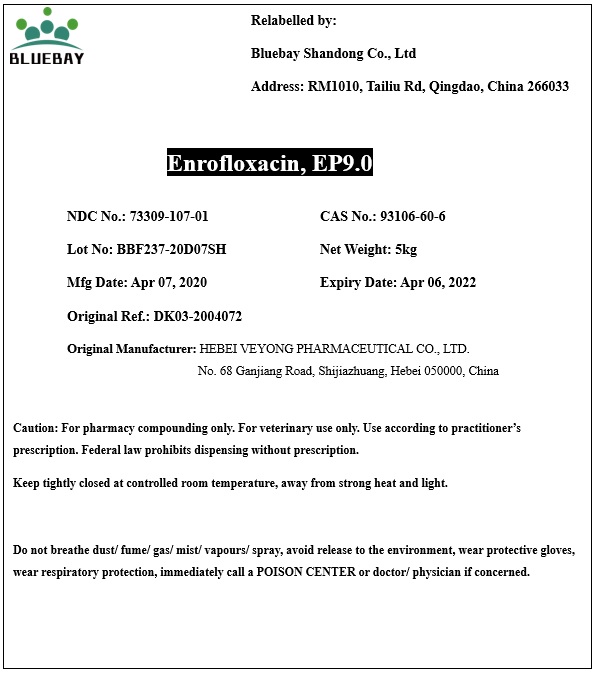 DRUG LABEL: Enrofloxacin
NDC: 73309-107 | Form: POWDER
Manufacturer: BLUEBAY SHANDONG CO.,LTD
Category: other | Type: BULK INGREDIENT
Date: 20200527

ACTIVE INGREDIENTS: ENROFLOXACIN 1 kg/1 kg

Enrofloxacin